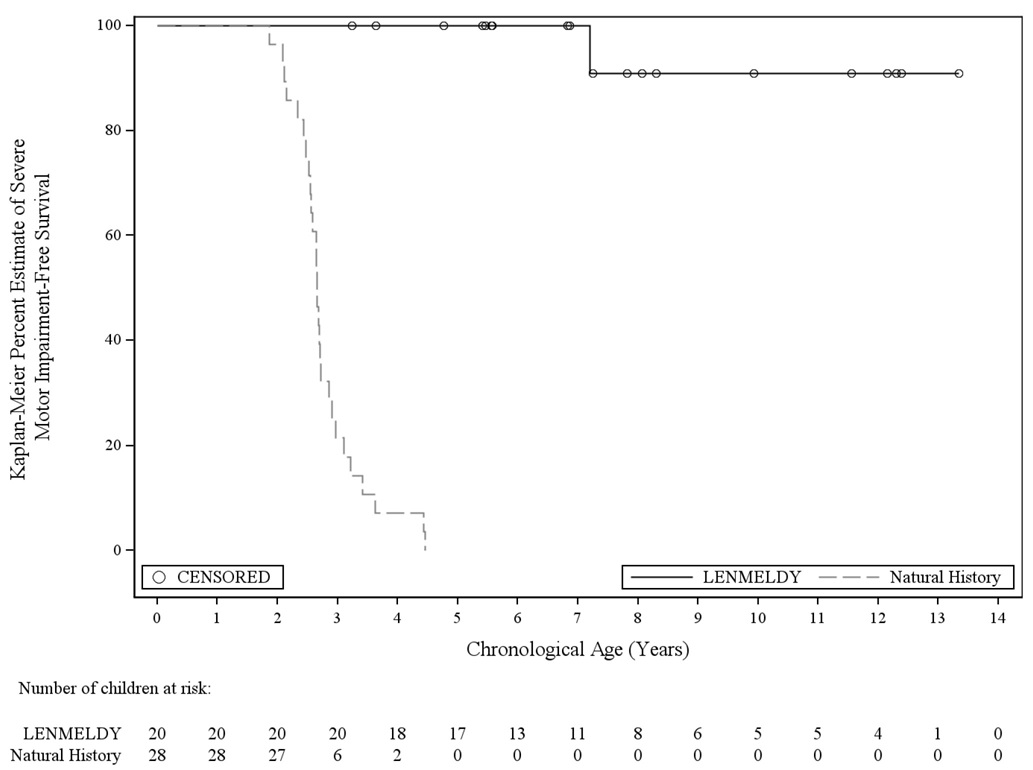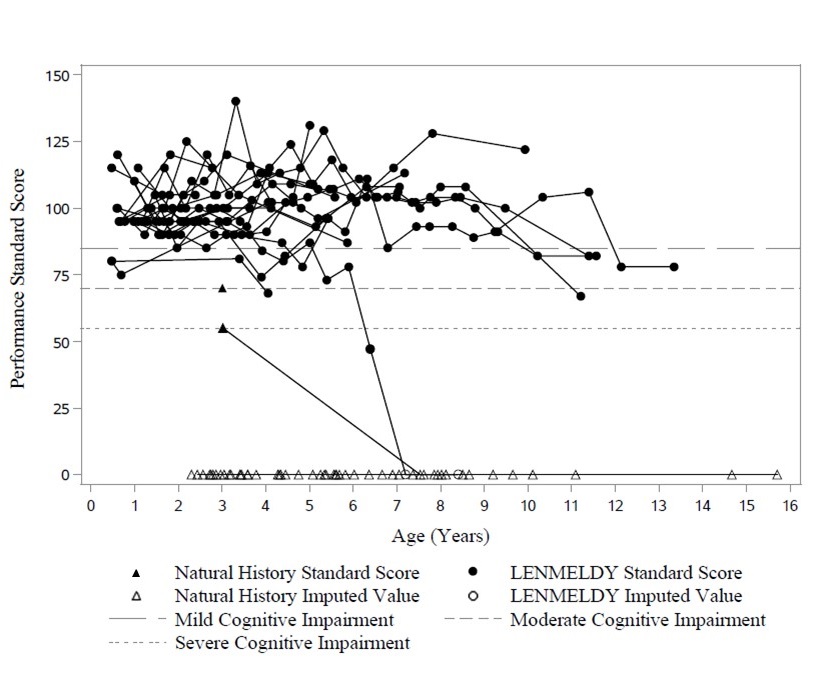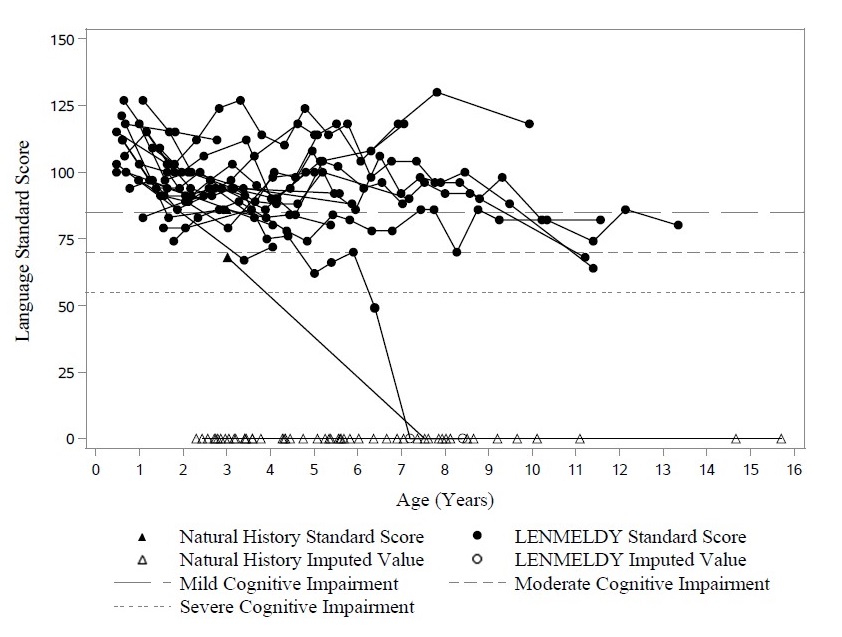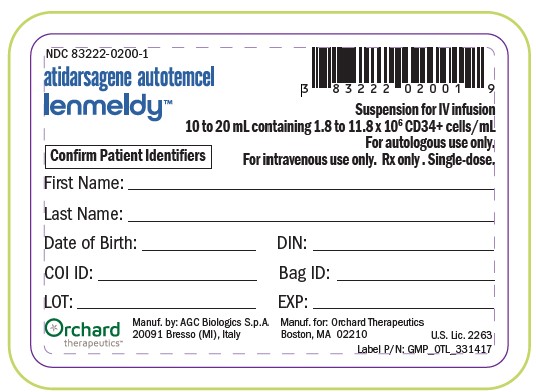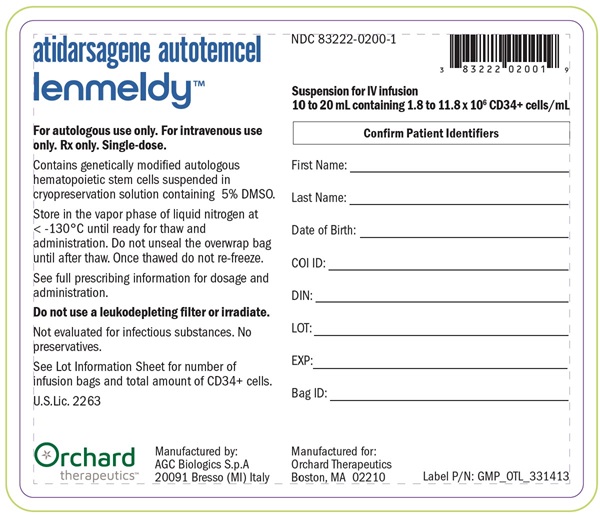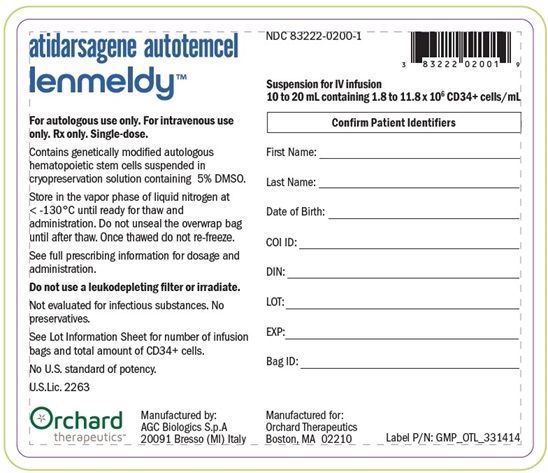 DRUG LABEL: LENMELDY
NDC: 83222-0200 | Form: SUSPENSION
Manufacturer: Orchard Therapeutics (Europe) Ltd
Category: other | Type: CELLULAR THERAPY
Date: 20250812

ACTIVE INGREDIENTS: ATIDARSAGENE AUTOTEMCEL 11800000 1/1 1
INACTIVE INGREDIENTS: ISOTONIC SODIUM CHLORIDE SOLUTION; DIMETHYL SULFOXIDE; ALBUMIN HUMAN

HIGHLIGHTS OF PRESCRIBING INFORMATION

These highlights do not include all the information needed to use LENMELDY safely and effectively.
See full prescribing information for LENMELDY.
LENMELDY (atidarsagene autotemcel) suspension for intravenous infusion
Initial U.S. Approval 2024

1 INDICATIONS AND USAGE

LENMELDY is an autologous hematopoietic stem cell-based gene therapyindicated for the treatment of children with pre-symptomatic late infantile (PSLI), pre-symptomatic early juvenile (PSEJ) or early symptomatic early juvenile (ESEJ) metachromatic leukodystrophy (MLD).

2 DOSAGE AND ADMINISTRATION

For autologous use only. For one-time single-dose intravenous use only.

- Children are required to undergo hematopoietic stem cell (HSC) mobilization followed by apheresis to obtain CD34+ cells for LENMELDY manufacturing. (2.2)
- Dosing of LENMELDY is based on the number of CD34+ cells in the infusion bag(s) per kg of body weight. (2.1)
- The minimum recommended dose is based on the MLD disease subtype. (2.1)
- Myeloablative conditioning must be administered before infusion of LENMELDY. (2.2)
- Confirm that the child’s identity matches the unique patient identification information on the LENMELDY infusion bag(s) prior to infusion. (2.2)
- Do not sample, alter, irradiate, or refreeze LENMELDY. (2.2)
- Do not use a leukodepleting filter. (2.3)

3 DOSAGE FORMS AND STRENGTHS

- LENMELDY is a single-dose cell suspension for intravenous infusion. (3)
- LENMELDY is composed of one to eight infusion bags which contain 2 to 11.8× 10^6cells/mL (1.8 to 11.8 x 10^6CD34^+cells/ml) suspended in cryopreservation solution. (3)

4 CONTRAINDICATIONS

- None (4)

5 WARNINGS AND PRECAUTIONS

- Thrombosis and Thromboembolic Events: Evaluate the risk factors for thrombosis prior to and after LENMEDLY infusion. Consider prophylaxis with anti-thrombotic agents prior to treatment with LENMELDY. (5.1)
- Encephalitis: Monitor children for signs or symptoms of encephalitis after treatment with LENMELDY. (5.2)
- Serious Infection: Monitor children for serious infection after myeloablative conditioning and LENMELDY infusion. (5.3)
- Veno-occlusive Disease: Monitor children for signs and symptoms of VOD including liver function tests in all patients during the first month after LENMELDY infusion. Consider prophylaxis for VOD. (5.4)
- Delayed Platelet Engraftment: Monitor children for thrombocytopenia and bleeding until platelet recovery is achieved. (5.5)
- Risk of Neutrophil Engraftment Failure: Monitor absolute neutrophil counts (ANC) after LENMELDY infusion. If neutrophil engraftment does not occur, administer rescue cells. (5.6)
- Risk of Insertional Oncogenesis:Monitor children for hematologic malignancies annually after treatment with LENMELDY. (5.7)
- Risk of Hypersensitivity Reactions: Monitor for hypersensitivity reactions during infusion. (5.8)

6 ADVERSE REACTIONS

- The most common non-laboratory adverse reactions (incidence ≥ 10%) were: febrile neutropenia (85%), stomatitis (77%), respiratory tract infections (54%), rash (33%), device related infections (31%), other viral infections (28%), pyrexia (21%), gastroenteritis (21%), and hepatomegaly (18%). (6.1)
- The most common laboratory abnormalities were: elevated D-dimer (67%), neutropenia (28%), and elevated liver enzymes (23%). (6.1)

To report SUSPECTED ADVERSE REACTIONS, contact Orchard Therapeutics at toll-free phone 1-888-878-0185 or FDA at 1-800-FDA-1088 or www.fda.gov/medwatch.

7 DRUG INTERACTIONS

- Anti-retrovirals: Do not take anti-retroviral medications for at least one month prior to initiating medications for stem cell mobilization and for the expected duration of time needed for the elimination of the medications. (7.2)

FULL PRESCRIBING INFORMATION

1 INDICATIONS AND USAGE

LENMELDY is indicated for the treatment of children with pre-symptomatic late infantile (PSLI), pre-symptomatic early juvenile (PSEJ) or early symptomatic early juvenile (ESEJ) metachromatic leukodystrophy (MLD).

2 DOSAGE AND ADMINISTRATION

For autologous use only. For one-time single-dose intravenous use only.

2.1 Dose

LENMELDY is provided as a single dose for infusion containing a suspension of CD34^+cells in one to eight infusion bags. Table 1 provides the minimum and maximum recommended dose of LENMELDY based on MLD disease subtype:

Table 1: Minimum and Maximum Recommended Dose of LENMELDY
MLD Subtype | Minimum Recommended Dose (CD34^+cells/kg) | Maximum Recommended Dose (CD34^+cells/kg)
Pre-symptomatic late infantile | 4.2 x 10^6 | 30 x 10^6
Pre-symptomatic early juvenile | 9 x 10^6 | 30 x 10^6
Early symptomatic early juvenile | 6.6 x 10^6 | 30 x 10^6

The dose administered is calculated based on the child’s weight at time of LENMELDY infusion using the information provided on the Lot Information Sheet. See the Lot Information Sheet provided with the product shipment for additional information pertaining to dose.

2.2 Preparation before LENMELDY Infusion

Mobilization, apheresis, and myeloablative conditioning are required prior to LENMELDY infusion. Before initiating these procedures, confirm that hematopoietic stem cell (HSC) gene therapy is appropriate for the child.

Screen children for hepatitis B virus (HBV), hepatitis C virus (HCV), human T-lymphotrophic virus 1 & 2 (HTLV-1/HTLV-2), human immunodeficiency virus 1 & 2 (HIV-1/HIV-2), cytomegalovirus (CMV), and mycoplasma infection in accordance with clinical guidelines before collection of cells for manufacturing.

Mobilization and Apheresis

Children are required to undergo HSC mobilization followed by apheresis to obtain CD34^+cells for LENMELDY manufacturing. In clinical trials of LENMELDY, granulocyte-colony stimulating factor (G-CSF) with or without plerixafor was used for mobilization.

For the manufacture of LENMELDY, a collection of a minimum of 8.0 × 10^6CD34^+cells/kg of autologous cells is required based on a weight at time of apheresis collection. Collection of the minimum number of CD34^+cells required for manufacture may be achieved using one or more cycles of mobilization.

A collection of unmanipulated back-up CD34^+cells of at least 2.0 × 10^6CD34^+cells/kg is required. These cells must be collected from the child and be cryopreserved prior to myeloablative conditioning. The back-up collection may be needed for rescue treatment if there is: 1) compromise of LENMELDY after initiation of conditioning but before infusion, 2) primary engraftment failure, or 3) loss of engraftment after infusion with LENMELDY. The back-up cells may be collected either through mobilized peripheral blood (mPB) apheresis or bone marrow collection.

Myeloablative Conditioning

Myeloablative conditioning must be administered before infusion of LENMELDY. In clinical trials of LENMELDY, busulfan was used for myeloablative conditioning. There is no data available supporting the use of alternative conditioning agents with LENMELDY.

Do not begin myeloablative conditioning until LENMELDY has been received and stored at the treatment center and the availability of the back-up collection of CD34^+cells has also been confirmed. After completion of the myeloablative conditioning, allow a minimum of 24 hours of washout before LENMELDY infusion.

Receipt and Storage of LENMELDY

- LENMELDY is shipped to the treatment center in the vapor phase of liquid nitrogen at less than -130°C (-202°F) along with the corresponding Lot Information Sheet. Two shippers would be used in the event that 5-8 bags are manufactured.
- Confirm patient identifiers on the product labels and the Lot Information Sheet.
- If there are any concerns about the product or packaging upon receipt, contact Orchard Therapeutics at 1-888-878-0185.
- Keep the infusion bag(s) in the metal cassette(s) and transfer LENMELDY from the transport vapor phase of liquid nitrogen shipper to the treatment center’s own vapor phase of liquid nitrogen storage at less than -130°C (-202°F). Store in the vapor phase of liquid nitrogen at less than -130°C (-202°F) until ready for thaw and administration.

Preparation of LENMELDY for Infusion

Coordinate the timing of LENMELDY thaw and infusion. Confirm the infusion time in advance and adjust the start time of LENMELDY thaw such that it will be available for infusion when the child and healthcare providers are ready to initiate LENMELDY administration as soon as possible after thaw. Each bag of LENMELDY should be infused via a central venous catheter and must be infused within 2 hours, post-thawing.

LENMELDY contains human blood cells that are genetically modified with replication-incompetent, self-inactivating lentiviral vector (LVV). Follow universal precautions and local biosafety guidelines for handling and disposal of LENMELDY to avoid potential transmission of infectious diseases.

Ensure the correct number of infusion bags are present. Use the corresponding Lot Information Sheet to confirm the number of LENMELDY bags shipped to the treatment center. A maximum of eight bags may be provided per child, which would take a maximum of approximately 16 hours to complete the infusion process. If more than one infusion bag is provided, thaw and administer each infusion bag completely before proceeding to thaw the next infusion bag. The following steps must be repeated for each LENMELDY infusion bag immediately prior to thaw.

1. Remove the metal cassette from the vapor phase of liquid nitrogen storage.
2. Confirm that "LENMELDY" is printed on the infusion bag label.
3. Confirm that the child's identity matches the unique patient identifiers located on the LENMELDY infusion bag. Do not infuse LENMELDY if the information on the patient-specific label on the infusion bag does not match the intended patient, and contact Orchard Therapeutics at 1-888-878-0185.
4. Use the accompanying Lot Information Sheet to confirm that the infusion bag is within the expiration date.
5. Inspect the infusion bag for any breaches of integrity before thawing and infusion. If an infusion bag is compromised, follow the local guidelines and contact Orchard Therapeutics immediately at 1-888-878-0185.
6. Thaw LENMELDY in the overwrap bag at 37°C (98.6°F) in a controlled thawing device. Once thawing is complete, the bag should be removed immediately from the thawing device. The overwrap bag should be carefully opened to remove the infusion bag which should be kept at room temperature until infusion.
7. After thawing, mix the contents gently by massaging the infusion bag to homogenize the cell suspension and disperse any remaining cell aggregates. If visible cell aggregates remain, continue to gently mix the contents of the bag. Most cell aggregates should disperse with gentle manual mixing. Do not shake the bag. Do not wash, spin down and/or resuspend LENMELDY in new media prior to infusion.

- Do not sample, alter, irradiate, or refreeze LENMELDY.

2.3 Administration

LENMELDY is for autologous use only. The child’s identity must match the patient identifiers on the LENMELDY cassette(s) and infusion bag(s). Do not infuse LENMELDY if the information on the patient-specific label does not match the intended patient. LENMELDY must not be irradiated or infused using a leukodepleting filter.

1. Before infusion, confirm that the child’s identity matches the unique patient identifiers on the LENMELDY infusion bag.Use the Lot Information Sheet to confirm the total number of infusion bags to be administered.
2. Prime the tubing of the infusion set with 0.9% sodium chloride solution prior to infusion.
3. Expose the sterile port on the infusion bag by tearing off the protective wrap covering the port.
4. Access the infusion bag and infuse LENMELDY as soon as possible after thawing and complete the infusion within 2 hours after thawing.
5. Administer each infusion bag of LENMELDY as an intravenous infusion via a central venous catheter within 30 minutes via gravity or infusion pump. An infusion flow rate should be calculated based on the volume in each infusion bag.
6. After the entire content of the infusion bag is infused, flush all LENMELDY remaining in the infusion bag and any associated tubing with 0.9% sodium chloride solution using a rinse volume that is equal to or greater than the priming volume of any intravenous infusion set used to ensure that as many cells as possible are infused into the child.
7. If more than one infusion bag is provided, administer the content of each infusion bag completely before proceeding to thaw (following Section 2.2steps 1-7) and infuse (following Section 2.3steps 1-6) the content of the next infusion bag. If more than one infusion bag is necessary, do not administer more than one bag of product per hour.

After LENMELDY Administration

Standard procedures for patient management after HSC transplantation should be followed after LENMELDY infusion.

- Irradiate any blood products required within the first 3 months after LENMELDY infusion.
- Children treated with LENMELDY should not donate blood, organs, tissues, or cells at any time in the future.

3 DOSAGE FORMS AND STRENGTHS

LENMELDY is a single-dose cell suspension for intravenous infusion.

LENMELDY is composed of one to eight infusion bags which contain 2 to 11.8 × 10^6cells/mL (1.8 to 11.8 x 10^6CD34^+cells/mL) suspended in cryopreservation solution [ see How Supplied/Storage and Handling (16)]. Each infusion bag contains 10 to 20 mL of LENMELDY.

See the Lot Information Sheet for actual dose.

4 CONTRAINDICATIONS

None.

5 WARNINGS AND PRECAUTIONS

5.1 Thrombosis and Thromboembolic Events

Treatment with LENMELDY may increase the risk of thrombosis and thromboembolic events. A child with PSEJ MLD died after experiencing a left hemisphere cerebral infarction secondary to a thrombotic event in a large blood vessel approximately one year after treatment with LENMELDY. Prior to the cerebral infarction, the child’s D-dimer was elevated (82 nmol/L, normal range: 1.5 - 4.2). Additional clinical findings included a minor elevation of liver enzymes. The etiology of the cerebral infarction was unclear but attribution to LENMELDY cannot be ruled out. No other events related to cerebral infarction have been reported during the clinical development of LENMELDY.

Some children received anti-thrombotic prophylaxis [ see Clinical Trials Experience (6.1)]. Evaluate the risk factors for thrombosis prior to and after LENMELDY infusion according to best clinical practice.

5.2 Encephalitis

Treatment with LENMELDY may increase the risk of encephalitis. A child with ESEJ MLD developed a serious event of encephalitis after treatment with LENMELDY. At the time of treatment, GMFC-MLD was Level 1 (able to walk independently with impaired gait). One month after treatment, the child experienced subacute neurological deterioration, with asthenia, hypotonia, cognitive and behavioral problems, vomiting, and swallowing disturbance. The child was afebrile, blood and CSF cultures were negative for bacterial infection, a large viral panel was negative and all routine laboratory tests were normal. The child was treated with plasmapheresis, immunoglobulin and rituximab leading to clinical improvement. Five months after onset of symptoms the child had reached GMFC-MLD Level 4 (walking not possible; able to sit without support and locomotion possible, or unable to sit without support but locomotion is possible). The child was subsequently treated with eculizumab and tocilizumab.

The etiology of this event is unclear but attribution to LENMELDY cannot be ruled out. Treatment with LENMELDY may trigger a relapsing-remitting pattern of disease progression. No other events related to encephalitis have been reported during the clinical development of LENMELDY.

Monitor children for signs or symptoms of encephalitis after LENMELDY treatment.

5.3 Serious Infection

In the period between start of conditioning and within one year after LENMELDY treatment, severe Grade 3 infections occurred in 39% of all children (21% bacterial, 5% viral, 5% bacterial and viral or bacterial and fungal, and 8% unspecified). The most common Grade 3 infections were device related infections (18%) (including two events of sepsis), respiratory tract infections (including 1 Grade 3 event of pneumonia) (8%), and gastroenteritis/enteritis (8%).

Grade 3 febrile neutropenia developed within 1 month after LENMELDY infusion in 82% of children. In the event of febrile neutropenia, monitor for signs and symptoms of infection and manage with broad-spectrum antibiotics, fluids, and other supportive care as medically indicated.

Monitor children for signs and symptoms of infection after myeloablative conditioning and LENMELDY infusion and treat appropriately. Administer prophylactic antimicrobials according to best clinical practice.

5.4 Veno-occlusive Disease

Three children (8%) treated in clinical trials of LENMELDY developed veno-occlusive disease (VOD), with one Grade 4 SAE and two Grade 3 AEs. None of these three events met Hy’s Law criteria.

Monitor children for signs and symptoms of VOD including liver function tests in all children during the first month after LENMELDY infusion. Consider prophylaxis for VOD with anti-thrombotic agents based on risk factors for VOD and best clinical practice.

5.5 Delayed Platelet Engraftment

Delayed platelet engraftment has been observed with LENMELDY treatment [ see Adverse Reactions (6.1)]. Bleeding risk is increased prior to platelet engraftment and may continue after engraftment in children with prolonged thrombocytopenia. In clinical trials of LENMELDY, 4 (10%) children had delayed platelet engraftment after day 60 (range day 67-109), with 3 children requiring platelet transfusions until engraftment occurred. All children treated with LENMELDY received transfusion support with platelets according to best clinical practice.

Inform children of the risk of bleeding until platelet recovery has been achieved. Monitor children for thrombocytopenia and bleeding.

5.6 Neutrophil Engraftment Failure

There is a potential risk of neutrophil engraftment failure after treatment with LENMELDY. In clinical trials of LENMELDY, no cases of neutrophil engraftment failure have been reported. Neutrophil engraftment failure is defined as failure to achieve three consecutive absolute neutrophil counts (ANC) ≥ 500 cells/microliter obtained on different days by Day 60 after infusion of LENMELDY.

Monitor neutrophil counts until engraftment has been achieved. If neutrophil engraftment failure occurs in a child treated with LENMELDY, provide rescue treatment with the unmanipulated back-up collection of CD34^+cells [ see Preparation before LENMELDY Infusion (2.2)].

5.7 Insertional Oncogenesis

There is a potential risk of LVV-mediated insertional oncogenesis after treatment with LENMELDY. In clinical trials of LENMELDY, no cases of insertional oncogenesis have been reported. Children treated with LENMELDY may develop hematologic malignancies and should be monitored lifelong. Monitor for hematologic malignancies with a complete blood count (with differential) annually and integration site analysis as warranted for at least 15 years after treatment with LENMELDY.

In the event that a malignancy occurs, contact Orchard Therapeutics at 1-888-878-0185 for reporting and to obtain instructions on collection of samples for testing.

5.8 Hypersensitivity Reactions

There is a potential risk of allergic reactions in children treated with LENMELDY. The dimethyl sulfoxide (DMSO) in LENMELDY may cause hypersensitivity reactions, including anaphylaxis which is potentially life-threatening and requires immediate intervention. Hypersensitivity including anaphylaxis can occur in children with and without prior exposure to DSMO. In clinical trials of LENMELDY, no cases of hypersensitivity reactions have been reported.

5.9 Anti-retroviral Use

Children should not take prophylactic HIV anti-retroviral medications for at least one month prior to mobilization, or for the expected duration of time needed for the elimination of the medications. Anti-retroviral medications may interfere with the manufacturing of LENMELDY. [ see Drug Interactions (7.2)].

If a child requires anti-retrovirals for HIV prophylaxis, initiation of LENMELDY treatment should be delayed until confirmation of a negative test for HIV.

5.10 Interference with Serology Testing

Children who have received LENMELDY are likely to test positive by polymerase chain reaction (PCR) assays for HIV due to LVV provirus insertion resulting in a false-positive test for HIV. Therefore, children who have received LENMELDY should not be screened for HIV infection using a PCR-based assay.

6 ADVERSE REACTIONS

The most common non-laboratory adverse reactions (occurring in ≥10% of all children within Year 1 of treatment) were: febrile neutropenia (85%), stomatitis (77%), respiratory tract infections (54%), rash (33%), device related infections (31%), other viral infections (28%), pyrexia (21%), gastroenteritis (21%), and hepatomegaly (18%).

The following clinically significant adverse reactions are described elsewhere in the labeling:

- Thrombosis and Thrombotic Events [ see Warnings and Precautions (5.1)]
- Encephalitis [ see Warnings and Precautions (5.2)]
- Serious Infection [ see Warnings and Precautions (5.3)]
- Veno-occlusive Disease [ see Warnings and Precautions (5.4)]
- Delayed Platelet Engraftment [ see Warnings and Precautions (5.5)]
- Neutrophil Engraftment Failure [ see Warnings and Precautions (5.6)]
- Insertional Oncogenesis [ see Warnings and Precautions (5.7)]
- Hypersensitivity Reactions [ see Warnings and Precautions (5.8)]

6.1 Clinical Trials Experience

Because clinical trials are conducted under widely varying conditions, adverse reaction rates observed in the clinical trials of a drug cannot be directly compared to rates in the clinical trials of another drug and may not reflect the rates observed in practice.

The safety data reflect experience from 39 children with MLD treated in clinical trials of LENMELDY: PSLI (n=20), PSEJ (n=7), ESEJ (n=10), and 2 children with advanced disease at the time of treatment [ see Clinical Studies (14)]. The median (min, max) years of follow-up for the safety population was 6.8 (0.6, 12.2).

Table 2 presents the non-laboratory treatment emergent adverse reactions occurring in ≥10% of all children with onset reported on or after the date of conditioning up to 1 year follow-up post-treatment.

Table 2: Summary of Non-Laboratory Treatment Emergent Adverse Reactions Reported in at Least 10% of Patients Within Year 1 Following Treatment with LENMELDY (N = 39) [Includes adverse events potentially related to busulfan myeloablative conditioning.]
Adverse reaction System Organ Class/Preferred Term | Any Grade n (%) patients | Grade 3 or higher n (%) patents
Blood and lymphatic system disorders | -- | --
Febrile neutropenia | 33 (85) | 32 (82)
Gastrointestinal disorders | -- | --
Stomatitis | 30 (77) | 29 (74)
General disorders and administration site conditions | -- | --
Pyrexia | 8 (21) | 1 (3)
Hepatobiliary disorders | -- | --
Hepatomegaly | 7 (18) | 0
Infections and infestations | -- | --
Respiratory tract infections [Includes events with PTs of Bronchitis, Nasopharyngitis, Pharyngitis, Pneumonia, Respiratory tract infection, Rhinitis, Tonsillitis, Upper respiratory fungal infection and Upper respiratory tract infection.] | 21 (54) | 3 (8)
Device related infection [Includes events of Bacterial sepsis, Catheter site cellulitis, Catheter site infection, Device related infection, Sepsis, and Vascular device infection.] | 12 (31) | 7 (18)
Gastroenteritis [Includes events with PTs of Enteritis, Gastroenteritis, Gastroenteritis Aeromonas and Gastroenteritis rotavirus.] | 8 (21) | 3 (8)
Other viral infections [Includes events with PTs of Adenovirus infection, Cytomegalovirus infection, Cytomegalovirus test positive, Cytomegalovirus viremia, Enterovirus infection, Hand-foot-and-mouth disease, Herpes zoster, SARSCov-2-test positive, and Viral infection (excluding PT of Gastroenteritis rotavirus).] | 11 (28) | 2 (5)
Skin and subcutaneous tissue disorders | -- | --
Rash [Includes events with PTs of Dermatitis, Dermatitis bullous, Rash, Rash erythematous, Drug eruption and Rash maculopapular.] | 13 (33) | 3 (8)

In clinical trials of LENMELDY, 11 children (28%) developed an adverse event of neutropenia following conditioning, 8 of which (21%) reported a Grade 3 event. Despite best clinical practices including transfusion to prevent severe anemia, three children (8%) developed an adverse event of anemia, 1 of which reported a Grade 3 event. Nine children (23%) developed elevated liver enzymes, including three children (8%) who developed a Grade 3 event. Elevated levels of D-dimer (greater than 4.2 nmol/L) have been reported in 26/39 (67%) children during clinical trials of LENMELDY. Abnormal values up to 109.5 nmol/L were identified at timepoints from Day 21 to Year 7 after LENMELDY infusion, with no pattern identified.

Other clinically important events that occurred in < 10% of the population included the following:

One child reported Grade 3 adverse reactions of elevated alanine- and aspartate transaminases which met the definition of Hy’s Law at day 14 after LENMELDY infusion and resolved without treatment by 9 months after initial onset. Two children reported Grade 3 elevations in liver enzymes, and 1 child reported Grade 1 elevations in liver enzymes. All events resolved without treatment and are considered related to conditioning.

7 DRUG INTERACTIONS

No formal drug interaction studies have been performed. LENMELDY is not expected to interact with the hepatic cytochrome P-450 family of enzymes or drug transporters.

7.1 Vaccines

The safety and effectiveness of vaccination during or following LENMELDY treatment have not been studied. Vaccination is not recommended during the 6 weeks preceding the start of myeloablative conditioning, and until hematological recovery following treatment with LENMELDY. Where feasible, administer childhood vaccinations prior to myeloablative conditioning for LENMELDY.

7.2 Anti-retrovirals

Children should not take anti-retroviral medications for at least one month prior to mobilization or the expected duration for elimination of the medications [ see Warnings and Precautions (5.5)]. Anti-retroviral medications may interfere with the manufacturing of LENMELDY.

8 USE IN SPECIFIC POPULATIONS

8.1 Pregnancy

Risk Summary

There are no clinical data from the use of LENMELDY in pregnant women. No animal reproductive and developmental toxicity studies have been conducted with LENMELDY to assess whether it can cause fetal harm when administered to a pregnant woman. LENMELDY must not be administered during pregnancy because of the risk associated with myeloablative conditioning. Pregnancy after LENMELDY infusion should be discussed with the treating physician.

In the U.S. general population, the estimated background risk of major birth defects and miscarriage in clinically recognized pregnancies is 2-4% and 15-20%, respectively.

8.2 Lactation

Risk Summary

There are no data on the presence of LENMELDY in human or animal milk, the effects on the breastfed child, or the effects on milk production. Because of the potential risks associated with myeloablative conditioning, breast-feeding should be discontinued during conditioning. The developmental and health benefits of breastfeeding should be considered along with the mother’s clinical need for LENMELDY and any potential adverse effects on the breastfed child from LENMELDY or from the underlying maternal condition. Breast-feeding after LENMELDY infusion should be discussed with the treating physician. Children receiving breast milk may continue to do so throughout their treatment under the advice of their treating physician.

8.3 Females and Males of Reproductive Potential

Pregnancy Testing

As a precautionary measure, a negative serum pregnancy test must be confirmed prior to the start of mobilization and re-confirmed prior to conditioning procedures and before administration of LENMELDY in females of childbearing potential.

Contraception

Males capable of fathering a child and females of childbearing age should use an effective method of contraception from start of mobilization through at least 6 months after administration of LENMELDY.

Infertility

There are no data on the effects of LENMELDY on fertility.

Data are available on the risk of infertility with myeloablative conditioning. In clinical trials of LENMELDY, seven children (50% of females) developed ovarian failure. Advise children of the option to cryopreserve semen or ova before treatment, if appropriate.

8.4 Pediatric Use

The safety and efficacy of LENMELDY has been established in children with PSLI, PSEJ and ESEJ MLD. The clinical trials of LENMELDY treated 20 PSLI, 7 PSEJ, and 10 ESEJ MLD children who received LENMELDY between ages 8 – 19 months (median age of 12 months), 11 months – 5.56 years (median age of 2.57 years), and 2.54 – 11.64 years (median age of 5.84 years), respectively. The safety and efficacy of LENMELDY have not yet been established in children with the late juvenile form of the disease [ see Clinical Studies (14)].

8.6 Patients Seropositive for Human Immunodeficiency Virus (HIV) or other infectious diseases

LENMELDY has not been studied in children with HIV-1, HIV-2, HTLV-1, HTLV-2, HBV, HVC, or mycoplasma infection. Negative serology tests for HIV-1/2, HTLV-1/2, HBV, HCV, and a negative test for mycoplasma are necessary to ensure acceptance of apheresis material for LENMELDY manufacturing.

8.7 Renal Impairment

LENMELDY has not been studied in children with renal impairment. Children should be assessed for renal impairment to ensure HSC transplantation is appropriate.

8.8 Hepatic Impairment

LENMELDY has not been studied in children with hepatic impairment. Children should be assessed for hepatic impairment to ensure HSC transplantation is appropriate.

11 DESCRIPTION

LENMELDY (atidarsagene autotemcel) is a gene therapy consisting of autologous CD34^+cells, containing hematopoietic stem cells (HSCs), transduced with a lentiviral vector (LVV) encoding the human arylsulfatase A (ARSA) gene, suspended in cryopreservation solution. LENMELDY is intended for one-time administration to add functional copies of the ARSA gene into the child’s own HSCs.

LENMELDY is prepared from the child’s own HSCs, which are collected via apheresis procedure(s). The autologous cells are enriched for CD34^+cells, then transduced ex vivowith a recombinant replication-incompetent self-inactivating (SIN) human immunodeficiency virus-1 (HIV-1) - based LVV that has been modified to carry the ARSA cDNA sequence under the human phosphoglycerate kinase (PGK) promoter. The transduced CD34^+cells are washed, formulated into a suspension, and then cryopreserved.

LENMELDY is manufactured for each individual child into infusion bags, which are cryopreserved before being thawed prior to administration [ see Dosage and Administration (2.2), How Supplied/Storage and Handling (16)]. The thawed product is a colorless to slightly yellow or pink cell suspension and may contain visible cell aggregates.

The formulation contains 5% (v/v) dimethyl sulfoxide (DMSO).

Each 1 mL of LENMELDY suspension for IV infusion contains 3.5 mg of sodium.

12 CLINICAL PHARMACOLOGY

12.1 Mechanism of Action

LENMELDY inserts one or more functional copies of the human ARSA complementary deoxyribonucleic acid (cDNA) into the patients’ HSCs, through transduction of autologous CD34^+cells with ARSA LVV. After LENMELDY infusion, transduced CD34^+HSCs engraft in bone marrow, repopulate the hematopoietic compartment and their progeny produce ARSA enzyme. Functional ARSA enzyme can breakdown or prevent the harmful accumulation of sulfatides.

12.2 Pharmacodynamics

Deficiency of ARSA is known to be the cause of MLD; therefore, ARSA activity in peripheral blood mononuclear cells of the hematopoietic lineage (i.e. ARSA in PBMC) was evaluated to provide evidence of pharmacodynamic activity of LENMELDY.

Median ARSA activity in PBMCs was at supranormal levels by 3 months post-treatment in the PSLI and PSEJ populations (normal range for ARSA activity is 31-198 nmol/mg/h) and supranormal median levels were sustained throughout the duration of follow-up (Table 3). In ESEJ median ARSA activity was within normal range from Month 3 to Year 2 and supranormal activity was achieved at Year 3 and 5 (Table 3).

Table 3: Summary of ARSA Activity (nmol/mg/h) in Total Peripheral Blood Mononuclear Cells by Visit in the Patients Treated with LENMELDY
Visit | Variable | PSLI (N=20) | PSEJ (N=7) | ESEJ (N=10)
Month 3 | Patient Samples, n | 18 | 6 | 10
-- | Median (Min, Max) | 682 (61, 3398) | 1140 (314, 1300) | 210 (50, 426)
Month 6 | Patient Samples, n | 16 | 6 | 7 [One value was below the lower limit of quantification (LLQ) or not detected or not quantifiable, and has been imputed as the LLQ (26 nmol/mg/h). Normal range for ARSA activity is 31-198 nmol/mg/h. ARSA=Arylsulfatase A; Max=Maximum; Min=Minimum. Number of children at timepoint represents the number of children with non-missing data (including those with imputed values).]
-- | Median (Min, Max) | 1095 (37, 2716) | 983 (150, 1804) | 107 (26, 444)
Year 1 | Patient Samples, n | 20 | 7 | 8
-- | Median (Min, Max) | 1239 (46, 6467) | 883 (272, 1976) | 130 (55, 688)
Year 2 | Patient Samples, n | 18 | 6 | 7
-- | Median (Min, Max) | 935 (26, 5935) | 1063 (328, 2205) | 82 (70, 219)
Year 3 | Patient Samples, n | 18 | 4 | 6
-- | Median (Min, Max) | 1558 (26, 7091) | 1156 (537, 2173) | 234 (30, 1271)
Year 5 | Patient Samples, n | 9 | 0 | 3
-- | Median (Min, Max) | 756 (28, 3474) | - | 363 (282, 793)

12.3 Pharmacokinetics

LENMELDY is an autologous gene therapy which includes hematopoietic stem cells (HSCs) that have been genetically modified ex vivo. The nature of LENMELDY is such that conventional pharmacokinetic studies on absorption, distribution, metabolism, and excretion are not applicable.

12.6 Immunogenicity

During the clinical development program, anti-ARSA antibodies (AAA) were reported in 6/39 children (5 PSLI and 1 PSEJ) with titers between 1:80 and 1:6400. Five events resolved between Days 45 and 368, of which two resolved spontaneously. One event was reported as ongoing. One child reported declining ARSA levels in the setting of AAA but the impact on clinical efficacy is unknown as the child is still in the pre-symptomatic phase of the disease. Four children received treatment with rituximab. There is insufficient information to characterize the impact of AAA on ARSA activity in PBMC, clinical efficacy, or safety.

13 NONCLINICAL TOXICOLOGY

13.1 Carcinogenesis, Mutagenesis, Impairment of Fertility

No carcinogenicity studies have been performed with LENMELDY. No studies have been conducted to evaluate the effects of LENMELDY on fertility.

14 CLINICAL STUDIES

The safety and efficacy of LENMELDY was assessed in 39 children across two single-arm, open-label clinical trials and a European Union (EU) expanded access program (EAP). Two children with advanced disease were excluded from the efficacy analysis. The clinical trials enrolled 13 children with PSLI, 6 children with PSEJ and 9 children with ESEJ MLD. The EU EAP enrolled 7 children with PSLI, 1 child with PSEJ and 1 child with ESEJ MLD. All children had documented biochemical and molecular diagnosis of MLD based on ARSA activity below the normal range and identification of two disease-causing ARSAalleles. In the case of a novel ARSAvariant(s), a 24-hour urine collection was required to show elevated sulfatide levels.

The major efficacy outcomes in clinical trials of LENMELDY were motor and neurocognitive function, as assessed by GMFC-MLD levels and standard scores on age-appropriate neurocognitive tests, respectively. The efficacy of LENMELDY was compared to an external untreated natural history (NHx) cohort of children with LI (n=28) and EJ (n=21) MLD. Data from the NHx cohort were collected both retrospectively and prospectively. Cognitive outcomes in the children with PSEJ and ESEJ MLD were compared to outcomes for untreated children reported in the medical literature.

In clinical trials of LENMELDY, children were classified as having PSLI, PSEJ, or ESEJ MLD based on the following criteria:

- PSLI MLD: Children with expected disease onset ≤ 30 months of age and an ARSAgenotype consistent with LI MLD. Pre-symptomatic status* defined as the absence of neurological signs and symptoms of MLD.
- PSEJ MLD: Children with expected disease onset > 30 months and <7 years of age and an ARSAgenotype consistent with EJ MLD. Pre-symptomatic status* defined as the absence of neurological signs and symptoms of MLD or physical exam findings limited to abnormal reflexes and/or clonus.
- ESEJ MLD: Children with disease onset > 30 months and <7 years of age and an ARSAgenotype consistent with EJ MLD. Early symptomatic status defined as walking independently (GMFC-MLD Level 0 with ataxia or GMFC-MLD Level 1) and IQ ≥ 85.

*Pre-symptomatic children were permitted to have abnormal reflexes or abnormalities on brain magnetic resonance imaging and/or nerve conduction tests not associated with functional impairment (e.g., no tremor, no peripheral ataxia).

Demographics and baseline characteristics for children who were included in the LENMELDY Integrated Summary of Efficacy analyses (n=37) are shown in Table 4.

Table 4: Demographics and Baseline Characteristics for Children with PSLI, PSEJ and ESEJ MLD Treated with LENMELDY (N=37)
Parameter | PSLI (N=20) | PSEJ (N=7) | ESEJ (N=10)
Age at Treatment (months) - Median (Min, Max) | 12 (8, 19) | 31 (11, 67) | 70 (31, 140)
Male – n (%) | 13 (65) | 6 (86) | 6 (60)
Race – n (%) | -- | -- | --
White/Caucasian | 18 (90) | 6 (86) | 10 (100)
Asian | 2 (10) | 0 | 0
Black or African American | 0 | 1 (14) | 0
Ethnicity - Hispanic or Latino – n (%) | 1 (5) | 0 | 0

HSC Collection:

HSCs used for the manufacture of LENMELDY were obtained by bone marrow (BM) collection (n=29), from apheresis collection of peripheral blood following the administration of HSC mobilizing agents (mPB) (n=8), or HSCs were obtained from both sources (n=2). Mobilization was achieved using G-CSF administered twice daily. From Day 3, plerixafor could be administered once daily. In the clinical trials of LENMELDY, plerixafor was administered to the 8 children where HSCs were obtained from apheresis collection only.

Pre-treatment Conditioning and Supportive Care:

All children received busulfan conditioning with a total dose range of 9 to 32 mg/kg and a target cumulative area under the curve (AUC) of 58,800 to 93,500 μg*h/L. Defibrotide was used in 11/39 children as prophylaxis for VOD. No additional anti-thrombotic agents were used as prophylaxis for VOD.

LENMELDY administration:

The ranges of doses administered associated with clinical efficacy are presented in Table 5.

Table 5: Doses of LENMELDY Associated with Clinical Efficacy in Children with PSLI, PSEJ, and ESEJ MLD
MLDSubtype | Median Dose (x 10^6CD34+ cells/kg) | Min, Max Dose (x 10^6CD34+ cells/kg) | Minimum Weight (kg) | Minimum Age at Treatment (months)
Pre-symptomatic late infantile | 14.2 | 4.2, 30 | 7.2 | 8
Pre-symptomatic early juvenile | 9.7 | 9, 30 | 14.5 | 43 [LENMELDY has been administered to children with PSEJ MLD from 12 months of age, but efficacy has not been determined due to limited follow up post-treatment.]
Early-symptomatic early juvenile | 9.5 | 6.6, 10.9 [Higher doses (up to 30 x 10 6 CD34+ cells/kg) have been administered to children with ESEJ MLD but efficacy has not been determined due to limited follow up post-treatment.] | - | -

One child with ESEJ MLD was treated with a dose of 6 x 10^6CD34^+cells/kg and did not show evidence of efficacy.

Comparison of LENMELDY Treatment with the Natural History of MLD in PSLI, PSEJ, and ESEJ

PSLI

Severe Motor Impairment-Free Survival (sMFS)

The primary endpoint was severe motor impairment-free survival, defined as the interval from birth to the first occurrence of loss of locomotion and loss of sitting without support (GMFC-MLD Level ≥ 5) or death. For analyses of the primary endpoint, an additional 2 untreated siblings not enrolled in the NHx study were included in the comparator group. Treatment with LENMELDY significantly extended severe motor impairment-free survival in children with PSLI MLD compared with untreated LI natural history children (Figure 1).

Figure 1: Kaplan-Meier Curve of Severe Motor Impairment-Free Survival for Children with PSLI MLD Treated with LENMELDY and LI Natural History Populations

- Seventeen children with PSLI MLD treated with LENMELDY have been followed until at least the age of 5 years. At the age of 5 years, 100% of LENMELDY treated PSLI children remained event-free compared with 0% of untreated LI children.
- Twelve out of 17 children who were at least 5 years of age at last follow-up (ages 5.4-13.3 years of age) retained independent ambulation (GMFC-MLD Level ≤ 1).
- Two children at the time of last assessment (ages 8.1 and 11.6 years) were able to ambulate with support (GMFC-MLD Level 2). Loss of ambulation without support occurred at 3.6 and 7.8 years of age, respectively.
- One child had progressed to GMFC-MLD Level 5 (loss of locomotion and loss of sitting without support; severe motor impairment) by age 7.2 years and lost all motor function (GMFC-MLD Level 6) at age 9.9 years.
- Two children never achieved independent ambulation.

Overall Survival

Treatment with LENMELDY significantly extends overall survival compared to untreated natural history. Fourteen treated children and 24 natural history children had sufficient follow-up to determine survival at 6 years from birth. At this timepoint, all patients treated with LENMELDY were alive, and 10 natural history children had died (42%).

Cognitive Function

Cognitive function was captured by neuropsychological tests (Bayley Scale of Infant Development [BSID], Wechsler Preschool and Primary Scale of Intelligence [WPPSI], Wechsler Intelligence Scale for Children [WISC] or Wechsler Adult Intelligence Scale [WAIS]), according to the child’s age and/or ability. Where required, due to the treated child’s severe decline and/or the limitations of the natural history evidence, developmental quotient scores were derived from age equivalent scores. When assessed within the appropriate age ranges, a standard score can be derived, allowing comparison of a child’s cognitive ability with the normative population. Cognitive function was defined using the following: normal cognitive function, standard score ≥ 85; mild cognitive impairment, standard score ≥ 70 and < 85; moderate cognitive impairment, score >55 and < 70; severe cognitive impairment, score ≤ 55.

Performance and language standard scores for children with PSLI MLD treated with LENMELDY compared to LI NHx children are presented in Figure 2 and Figure 3, respectively. Where a child has been assessed utilizing an age-appropriate test, and a standard score has been obtained, these are presented as closed circles for children with PSLI MLD treated with LENMELDY and as closed triangles for LI NHx children. Where an age appropriate standard score could not be obtained due to cognitive impairment, the standard score has been imputed as zero (open circles for children with PSLI MLD treated with LENMELDY and open triangles for LI NHx children).

Nineteen of 20 children with PSLI MLD had performance standard scores above the threshold of severe cognitive impairment (performance standard score > 55) through to the last follow-up. At last assessment, two of these children were below the threshold for moderate cognitive impairment (< 70), with all others maintaining performance standard scores ≥ 70 and most maintaining normal scores (≥ 85). This contrasts markedly with results in LI NHx children with completed neuropsychological assessments who demonstrate severe cognitive impairment early in their disease course (Figure 2).

Figure 2: Plot of Performance Standard Score vs. Age (PSLI) LENMELDY and LI Natural History Populations

Note: Performance standard scores have been imputed as zero in cases where they could not be derived due to severe cognitive impairment.

Nineteen of 20 children with PSLI MLD treated with LENMELDY had language standard scores above the threshold of severe impairment (language standard scores > 55) at last follow-up. At last assessment, two of these children were just below the threshold for moderate impairment (< 70), with all others maintaining language standard scores ≥ 70 and most maintaining normal scores (≥ 85). This contrasts markedly with results in LI NHx children with completed neuropsychological assessments who demonstrate severe impairment early in their disease course (Figure 3).

Figure 3: Plot of Language Standard Score vs. Age (PSLI) LENMELDY and LI Natural History Populations

Note: Language standard scores have been imputed as zero in cases where they could not be derived due to severe cognitive impairment.

PSEJ

Seven children with PSEJ MLD were treated with LENMELDY. One child died at age 2.1 years from a cerebral infarction. There were insufficient data in three children who were too young at last follow-up to evaluate efficacy of LENMELDY as symptom onset may not begin until 7 years of age in EJ MLD. Two children had evaluable motor and cognitive outcomes. One child had evaluable motor outcomes, but while showing stable normal cognitive function, was neither old enough nor had sibling data for cognitive events to be evaluable.

Motor Function

Three of seven children had evaluable motor outcomes:

- One child treated at 4.1 years of age retained normal gait (GMFC-MLD Level 0) at age 11.9 years. Their matched sibling comparator lost all motor function (GMFC-MLD Level 6) by age 6 years.
- One child treated at 3.6 years of age retained normal gait (GMFC-MLD Level 0) at age 7.3 years. Their matched sibling comparator developed impaired gait (GMFC-MLD Level 1) at age 5 years.
- One child treated at 5.6 years of age retained normal gait (GMFC-MLD Level 0) until age 12.8 years and still had independent ambulation (GMFC-MLD Level 1) at 13.6 years of age.

Cognitive Function

Two of seven children with PSEJ had evaluable cognitive function:

- One child treated at 4.1 years of age retained stable normal cognitive function (performance and language standard scores of 130 and 122, respectively) at age 11.9 years.
- One child treated at 5.6 years of age retained stable normal performance standard score (116 at 11.4 years). While language standard score remained normal (86 at 11.4 years), it declined from 102 at baseline.

ESEJ

Motor and cognitive outcomes for children with ESEJ MLD treated with LENMELDY are presented in Table 6.

Table 6: Motor and Cognitive Outcomes for Children with ESEJ MLD Treated with LENMELDY
Patient | Age at Baseline (Years) | Baseline Score [Motor = GMFC-MLD score where Level 0 = walking without support quality of performance normal for age; Level 1 = walking without support but with reduced quality of performance; Level 2 = walking with support, walking without support not possible; Level 3 = sitting without support and locomotion such as crawling or rolling, walking without support not possible; Level 4 = sitting without support but no locomotion or sitting without support not possible but locomotion such as crawling or rolling; Level 5 = no locomotion nor sitting without support but head control is possible; Level 6 = loss of any locomotion as well as loss of any head and trunk control.] , [Language = Language standard score.] , [Performance = Performance standard score; obtained on age-appropriate neuropsychological assessments, where normal cognitive function, standard score ≥ 85; mild cognitive impairment, standard score ≥ 70 and < 85; moderate cognitive impairment, standard score >55 and < 70; severe cognitive impairment, standard score ≤ 55.] | Age at Last Assessment (Years) | Last Assessment Score
Patient 1 | 3.2 | Motor Level 1 | 12.7 | Motor Level 5
-- | 3.2 | Language = 103 Performance = 100 | 7.3 | Language = 46 Performance = 56
Patient 2 | 7.3 | Motor Level 0 | 15.5 | Motor Level 5
-- | 7.3 | Language = 110 Performance = 119 | 15.5 | Language = 82 Performance = 87
Patient 3 [Patient 3 and Patient 10 had a mild EJ MLD phenotype at baseline.] | 11.6 | Motor Level 1 | 19.1 | Motor Level 3
-- | 11.6 | Language = 92 Performance = 119 | 15.8 | Language = 96 Performance = 135
Patient 4 | 7.0 | Motor Level 1 | 14.2 | Motor Level 3
-- | 7.0 | Language = 104 Performance = 89 | 11.0 | Language = 92 Performance = 93
Patient 5 | 5.7 | Motor Level 1 | 6.5 | Motor Level 5
-- | 5.7 | Language = 102 Performance = 82 | Died [Patients 5 and 7 died due to disease progression.] age 7 years: N/A | Language/ Performance not assessed due to patient death.
Patient 6 | 5.5 | Motor Level 0 | 12.5 | Motor Level 4
-- | 5.5 | Language = 118 Performance = 115 | 9.6 (attempted) | Unable to assess after 7.4 years due to disease progression.
Patient 7 | 5.9 | Motor Level 1 | 6.1 | Motor Level 2
-- | 5.9 | Language = 112 Performance = 87 | Died age 6.6 years: N/A | Language/ Performance not assessed due to patient death.
Patient 8 | 4.5 | Motor Level 0 | 7.0 | Motor Level 0
-- | 4.5 | Language = 122 Performance = 129 | 6.5 | Language = 110 Performance = 128
Patient 9 | 2.5 | Motor Level 0 | 5.1 | Motor Level 1
-- | 2.5 | Language = 94 Performance = 120 | 4.6 | Language = 78 Performance = 89
Patient 10 | 7.6 | Motor Level 0 | 16.5 | Motor Level 2
-- | 7.5 | Language = 97 Performance = 87 | 14.3 | Language = 80 Performance = 95

Note: Age at baseline is the age of the child at the last assessment prior to the time of treatment with LENMELDY.

Four children (Patients 2, 3, 4, and 10) with ESEJ MLD had favorable cognitive outcomes after treatment in the setting of motor decline. Retention of cognitive functioning has not been reported in this phase of EJ MLD disease, as motor and cognitive functioning typically decline together in untreated children.

Gallbladder Disease in Children with PSLI, PSEJ, and ESEJ Treated with LENMELDY

Of the 28 children who had pre-existing gallbladder disease, 14 (50%) had persistent MLD gallbladder disease (regardless of disease subtype) following treatment with LENMELDY. Five children treated with LENMELDY developed gallbladder disease after treatment (regardless of disease subtype).

15 REFERENCES

^1Kehrer C, Elgün S, Raabe C, Böhringer J, Beck-Wödl S, Bevot A, et al. Association of age at onset and first symptoms with disease progression in patients with metachromatic leukodystrophy. Neurology. 2021;96(2):e255-66.

^2Fumagalli F, Zambon AA, Rancoita PMV, Baldoli C, Canale S, Spiga I, et al. Metachromatic leukodystrophy: a single-center longitudinal study of 45 patients. J Inherit Metab Dis. 2021;1-14.

^3MacFaul R, Cavanagh N, Lake BD, Stephens R, Whitefield AE. Metachromatic leukodystrophy: review of 38 cases. Arch Dis Child. 1982;57:168-175.

^4Kehrer C, Groeschel S, Kustermann-Kuhn B, Bürger F, Köhler W, Kohlschütter A, et al. Language and cognition in children with metachromatic leukodystrophy: onset and natural course in a nationwide cohort. Orphanet J Rare Dis. 2014;9:18.

16 HOW SUPPLIED/STORAGE AND HANDLING

LENMELDY is supplied in up to eight infusion bags containing a frozen suspension of genetically modified autologous cells enriched for CD34^+cells. Each bag contains 10 to 20 mL of suspension. Each infusion bag is individually packed within an overwrap in a metal cassette. LENMELDY is shipped from the manufacturing facility to the treatment center storage facility in one to two cryoshipper(s), which may contain multiple metal cassettes intended for a single child. Two shippers would be used in the event that 5-8 bags are manufactured. A Lot Information Sheet is affixed inside the shipper.

- 50 mL infusion bag, overwrap, and metal cassette (NDC 83222-0200-1).

Match the identity of the child with the patient identifiers on the metal cassette(s), infusion bag(s), and Lot Information Sheet upon receipt.

- Store LENMELDY in the vapor phase of liquid nitrogen at less than -130°C (-202°F) until ready for thaw and administration.
- Thaw LENMELDY prior to infusion [ see Dosage and Administration (2)].
- Do not re-freeze after thawing.
- Do not irradiate LENMELDY, as this could lead to inactivation.

17 PATIENT COUNSELING INFORMATION

Ensure that patients and/or caregivers understand the risk of manufacturing failure. A collection of unmanipulated back-up CD34^+cells is required in case of manufacturing failure. These cells must be collected from the patient and be cryopreserved prior to myeloablative conditioning [ see Preparation before LENMELDY Infusion (2.2)].

Prior to treatment, advise patients and/or caregivers of the following:

- Risks associated with mobilization and myeloablative conditioning agents [ see Preparation before LENMELDY Infusion (2.2), Use in Specific Populations(8.1, 8.3) ].
- Risk of Hypersensitivity Reactions - Although no cases have been reported to date, allergic reactions may occur with the infusion of LENMELDY. The dimethyl sulfoxide (DMSO) in LENMELDY may cause hypersensitivity reactions, including anaphylaxis [ see Warnings and Precautions (5.4)].

After treatment, advise patients and/or caregivers of the following:

- Thrombosis and Thrombotic Event-A risk of blood clots may occur. Monitor patients for signs and symptoms of thrombosis [ see Warnings and Precautions (5.1)].
- Encephalitis- Monitor patients for signs or symptoms of encephalitis, including neurological deterioration such as weakness, decreased muscle tone, cognitive deterioration, behavioral problems, vomiting, and swallowing difficulties [ see Warnings and Precautions (5.2)].
- Serious Infection- Life-threatening bacterial and viral infections may occur. Monitor patients for signs and symptoms of infection [ see Warnings and Precautions (5.3)].
- Veno-occlusive Disease- Blood sampling will occur before and after LENMELDY infusion to monitor for liver problems including severe, life threatening, veno-occlusive disease [ see Warnings and Precautions (5.4)].
- Delayed Platelet Engraftment- A risk of bleeding exists after myeloablative conditioning and before platelet engraftment and may continue after engraftment in patients who have continued thrombocytopenia [ see Warnings and Precautions (5.5)].
- Neutrophil Engraftment Failure- There is a potential risk of neutrophil engraftment failure and the need for rescue treatment with their back-up collection of CD34^+cells [ see Warnings and Precautions (5.6)].
- Insertional Oncogenesis-There is a potential risk of insertional oncogenesis after treatment with LENMELDY. Patients should be monitored lifelong. Monitoring will include assessment for hematologic malignancies annually for at least 15 years after treatment with LENMELDY. This will include integration site analysis as warranted [ see Warnings and Precautions (5.7)].

Advise patients and/or caregivers to seek immediate attention for the following:

- Signs of a blood clot, which may include pain, discoloration, or swelling of an arm, legs or feet, with warmth over the affected area, unexplained shortness of breath, acute chest pain or discomfort that worsens on deep breathing, unexplained rapid pulse, numbness or weakness on one side of the body [ see Warnings and Precautions (5.1)].
- New or worsening bleeding or bruising. Platelet recovery following LENMELDY infusion could be delayed, potentially resulting in an increased risk of bruising or bleeding until platelet recovery has been achieved [ see Warnings and Precautions (5.5)].

Advise patients and/or caregivers to:

- Monitor for signs and symptoms of bleeding and have frequent blood draws for platelet counts, until platelet recovery has been achieved [ see Warnings and Precautions (5.5)].
- Have their treating physician contact Orchard Therapeutics at 1-888-878-0185 if they are diagnosed with a malignancy [ see Warnings and Precautions (5.7)] or a blood clot [ see Warnings and Precautions (5.3)].

Advise patients and/or caregivers that patients should not donate blood, organs, tissues, or cells at any time in the future [ see Dosage and Administration (2.3)].

Advise patients and/or caregivers that treatment with LENMELDY may cause a false-positive human immunodeficiency virus (HIV) test result if tested using a PCR assay [ see Warnings and Precautions (5.10)].

Manufactured for:
Orchard Therapeutics North America
Boston, MA 02210
US License No 2263

Lenmeldy is a trademark of Orchard Therapeutics plc.

PACKAGE LABEL.PRINCIPAL DISPLAY PANEL

NDC 83222-0200-1
atidarsagene autotemcel
lenmeldy™
Suspension for IV infusion
10 to 20mL containing 1.8 to 11.8 x 10^6 CD34+ cell/mL
For autologous use only.
For intravenous use only. Rx only. Single-dose.
Confirm Patient Identifiers
First Name:______
Last Name:______
Date of Birth: ______ DIN: ______
COI ID: ______ Bag ID: ______
LOT: ______ EXP: ______
Orchard
therapeutics™
Manuf. by: AGC Biologics S.p.A.
20091 Bresso (MI), Italy
Manuf. for: Orchard Therapeutics
Boston, MA 02210
U.S. Lic. 2263
Label P/N: GMP_OTL_331417

NDC 83222-0200-1
atidarsagene autotemcel
lenmeldy™
Suspension for IV infusion
10 to 20mL containing 1.8 to 11.8 x 10^6 CD34+ cell/mL
For autologous use only. For intravenous use
only. Rx only. Single-dose.
Confirm Patient Identifiers
Contains genetically modified autologous
hematopoietic stem cells suspended in
cryopreservastion solution containing 5% DMSO.
Store in the vapor phase of liquid nitrogen at
< -130°C until ready for thaw and
administration. Do not unseal the overwrap bag
until after thaw. Once thawed do not re-freeze.
See full prescribing information for dosage and
administration.
Do not use a leukodepleting filter or irradiate.
Not evaluated for infectious substances. No
preservatives.
See Lot Information Sheet for number of
infusion bags and total amount of CD34+ cells.
U.S.Lic. 2263
First Name:______
Last Name:______
Date of Birth: ______
COI ID: ______
DIN: ______
LOT: ______
EXP: ______
Bag ID: ______
Orchard
therapeutics™
Manufactured by:
AGC Biologics S.p.A.
20091 Bresso (MI), Italy
Manufactured for:
Orchard Therapeutics
Boston, MA 02210
Label P/N: GMP_OTL_331413

NDC 83222-0200-1
atidarsagene autotemcel
lenmeldy™
Suspension for IV infusion
10 to 20mL containing 1.8 to 11.8 x 10^6 CD34+ cell/mL
For autologous use only. For intravenous use
only. Rx only. Single-dose.
Confirm Patient Identifiers
Contains genetically modified autologous
hematopoietic stem cells suspended in
cryopreservastion solution containing 5% DMSO.
Store in the vapor phase of liquid nitrogen at
< -130°C until ready for thaw and
administration. Do not unseal the overwrap bag
until after thaw. Once thawed do not re-freeze.
See full prescribing information for dosage and
administration.
Do not use a leukodepleting filter or irradiate.
Not evaluated for infectious substances. No
preservatives.
See Lot Information Sheet for number of infusion
bags and total amount of CD34+ cells.
No U.S. standard of potency.
U.S.Lic. 2263
First Name:______
Last Name:______
Date of Birth: ______
COI ID: ______
DIN: ______
LOT: ______
EXP: ______
Bag ID: ______
Orchard
therapeutics™
Manufactured by:
AGC Biologics S.p.A.
20091 Bresso (MI), Italy
Manufactured for:
Orchard Therapeutics
Boston, MA 02210
Label P/N: GMP_OTL_331414